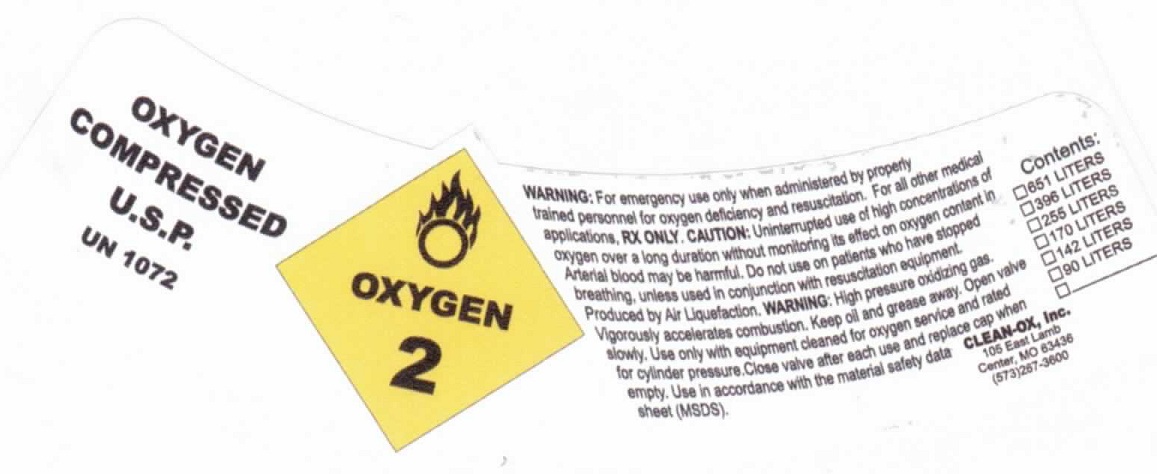 DRUG LABEL: OXYGEN, COMPRESSED
NDC: 43555-020 | Form: GAS
Manufacturer: CLEAN-OX, INC
Category: prescription | Type: HUMAN PRESCRIPTION DRUG LABEL
Date: 20100816

ACTIVE INGREDIENTS: OXYGEN 1 L/1 L

OXYGEN COMPRESSED U.S.P. UN 1072

PACKAGE LABEL

WARNINGS: for emergency use only when administered by properly trained personnel for oxygen deficiency and resuscitation. for all other medical applications, RX ONLY. CAUTION: Uninterrupted use of high concentrations of oxyggen over a long duration without monitoring its effect on oxygen cotnent in arterial blood may be harmful. Do not use on patients who have stopped breathing, unless used in conjunction with resucscitation equipment. Producted by Air Liquefaction. WARNING: High pressure oxidizing gas. Vigorously accelerates combustion. Keep oil and grease away. Open valve slowly. Use only with equipment cleared for oxyten service and rated for cylinder pressure. Close valve after each use and replace cap when empty. Use in accordance withthe material safety data sheet (MSDS).

CLEAN-OX, Inc.
105 East Lamb
Center, MO 63436
(573)-267-3600

contents:

651 liters

395 liters

233 liters

170 liters

142 liters

90 liters